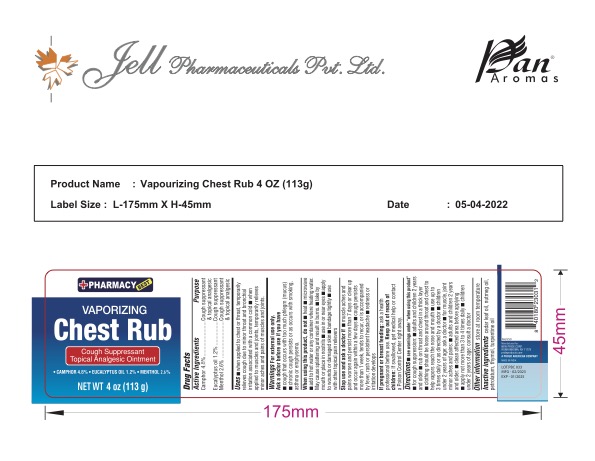 DRUG LABEL: Vaporising Chest Rub
NDC: 58037-010 | Form: CREAM
Manufacturer: New Pride Corp
Category: otc | Type: HUMAN OTC DRUG LABEL
Date: 20241219

ACTIVE INGREDIENTS: CAMPHOR (SYNTHETIC) 4.8 g/100 g; MENTHOL 2.6 g/100 g; EUCALYPTUS OIL 1.2 g/100 g
INACTIVE INGREDIENTS: CEDAR LEAF OIL; NUTMEG OIL; PARAFFIN; PETROLATUM; THYMOL; TURPENTINE

Vaporising chest rub

Active Ingredients Purpose

Menthol 2.6% Cough supressant/Topical Analgesic

Camphor 4.8% Cough supressant/Topical Analgesic

Eucalyptus oil 1.2% Cough Supressant

PURPOSE

Uses Temporarily relieves throat and chest

- cough

- nasal congestion due to common cold

- aching muscles

- minor aches and pains

Keep out of reach of children. In case of of accidental ingestion, get medical help or contact a Poison Control Center immediately.

Stop use and ask a doctor if

muscle aches/pains persist for more than 7 days or come back

cough lasts more than 7 days, comes back, or occurs with fever, rash, or headache that lasts. Thes could be signs of a serious condition

Warnings

For external use only

Do not use

- by mouth

- in nostrils

- on wounds or damaged skin

- with light bandages

Ask a doctor before use if you have

- asthma

- excessive phlegm (mucus)

- emphysema

- persistant or chronic cough

- cough associated with smoking

When using this product do not

- heat

- microwave

- use near open flame

- add to hot water or any container where heating water may cause splattering and result in burns

If pregnant or breat feeding, ask a health professional before use

Directions

- see important warnings under "When Using this product"

- children under 2 years of age, ask a doctor before using the product

- Adults and children 2 years and older. rub a thick layer of on chest and throat or rub on sore aching muscles. If desired cover with a dry soft cloth but keep clothing loose. Repeat up to 3 times daily

Other information Store at room temperature

Inactive ingredients cedar leaf oil, nutmeg oil, paraffin, petrolatum, thymol, turpentine oil